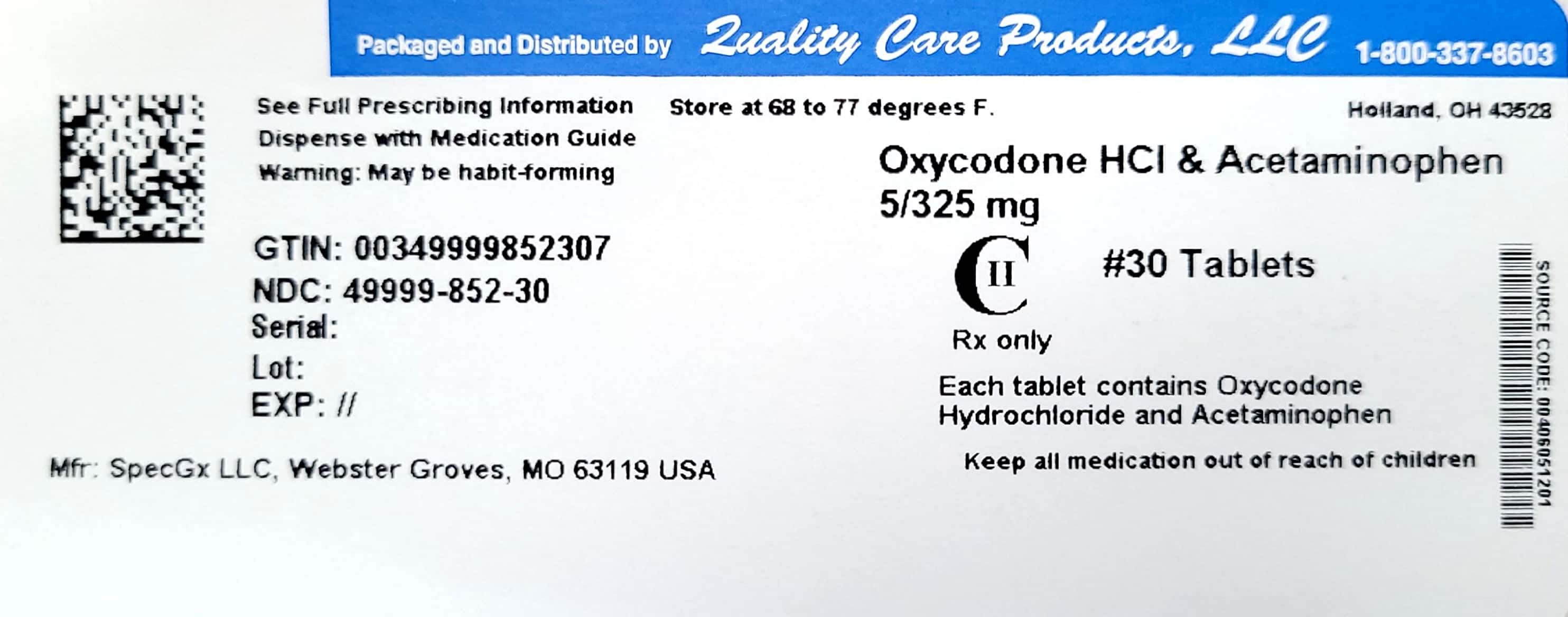 DRUG LABEL: Oxycodone and Acetaminophen
NDC: 49999-852 | Form: TABLET
Manufacturer: Quality Care products LLC
Category: prescription | Type: HUMAN PRESCRIPTION DRUG LABEL
Date: 20241216
DEA Schedule: CII

ACTIVE INGREDIENTS: OXYCODONE HYDROCHLORIDE 5 mg/1 1; ACETAMINOPHEN 325 mg/1 1
INACTIVE INGREDIENTS: CROSPOVIDONE; CELLULOSE, MICROCRYSTALLINE; POVIDONE; STARCH, CORN; SILICON DIOXIDE; STEARIC ACID

Oxycodone APAP 5mg 325mg

DESCRIPTION
Each tablet, for oral administration, contains oxycodone hydrochloride and acetaminophen in the following strengths:
Oxycodone Hydrochloride USP ..........................................................................5 mg* Acetaminophen USP ........................................................................................325 mg *5 mg oxycodone HCl is equivalent to 4.4815 mg of oxycodone. Oxycodone Hydrochloride USP .......................................................................7.5 mg* Acetaminophen USP ........................................................................................325 mg *7.5 mg oxycodone HCl is equivalent to 6.7228 mg of oxycodone. Oxycodone Hydrochloride USP .......................................................................7.5 mg* Acetaminophen USP ........................................................................................500 mg *7.5 mg oxycodone HCl is equivalent to 6.7228 mg of oxycodone. Oxycodone Hydrochloride USP .........................................................................10 mg* Acetaminophen USP .........................................................................................325 mg *10 mg oxycodone HCl is equivalent to 8.9637 mg of oxycodone.All strengths of oxycodone and acetaminophen tablets USP also contain the following inactive ingredients: crospovidone, microcrystalline cellulose, povidone, pregelatinized starch, silicon dioxide and stearic acid.
Oxycodone, 4,5α-epoxy-14-hydroxy-3-methoxy-17-methylmorphinan-6-one hydrochloride, is a semisynthetic opioid analgesic which occurs as a white, odorless, crystalline powder having a saline, bitter taste. It is derived from the opium alkaloid thebaine. Oxycodone hydrochloride may be represented by the following structural formula:
Acetaminophen, 4'-hydroxyacetanilide, is a non-opiate, non-salicylate analgesic and antipyretic which occurs as a white, odorless, crystalline powder, possessing a slightly bitter taste. It may be represented by the following structural formula:

CLINICAL PHARMACOLOGY
Central Nervous System
Oxycodone is a semisynthetic pure opioid agonist whose principal therapeutic action is analgesia. Other pharmacological effects of oxycodone include anxiolysis, euphoria and feelings of relaxation. These effects are mediated by receptors (notably μ and κ) in the central nervous system for endogenous opioid-like compounds such as endorphins and enkephalins. Oxycodone produces respiratory depression through direct activity at respiratory centers in the brain stem and depresses the cough reflex by direct effect on the center of the medulla.
Acetaminophen is a non-opiate, non-salicylate analgesic and antipyretic. The site and mechanism for the analgesic effect of acetaminophen has not been determined. The antipyretic effect of acetaminophen is accomplished through the inhibition of endogenous pyrogen action on the hypothalamic heat-regulating centers.
Gastrointestinal Tract and Other Smooth Muscle
Oxycodone reduces motility by increasing smooth muscle tone in the stomach and duodenum. In the small intestine, digestion of food is delayed by decreases in propulsive contractions. Other opioid effects include contraction of biliary tract smooth muscle, spasm of the Sphincter of Oddi, increased ureteral and bladder sphincter tone, and a reduction in uterine tone.
Cardiovascular System
Oxycodone may produce a release of histamine and may be associated with orthostatic hypotension, and other symptoms, such as pruritus, flushing, red eyes, and sweating.
Pharmacokinetics
Absorption and Distribution – The mean absolute oral bioavailability of oxycodone in cancer patients was reported to be about 87%. Oxycodone has been shown to be 45% bound to human plasma proteins in vitro. The volume of distribution after intravenous administration is 211.9 ± 186.6 L.
Absorption of acetaminophen is rapid and almost complete from the GI tract after oral administration. With overdosage, absorption is complete in 4 hours. Acetaminophen is relatively uniformly distributed throughout most body fluids. Binding of the drug to plasma proteins is variable; only 20% to 50% may be bound at the concentrations encountered during acute intoxication.
Metabolism and Elimination
A high portion of oxycodone is N-dealkylated to noroxycodone during first-pass metabolism. Oxymorphone, is formed by the O-demethylation of oxycodone. The metabolism of oxycodone to oxymorphone is catalyzed by CYP2D6. Free and conjugated noroxycodone, free and conjugated oxycodone, and oxymorphone are excreted in human urine following a single oral dose of oxycodone. Approximately 8% to 14% of the dose is excreted as free oxycodone over 24 hours after administration. Following a single, oral dose of oxycodone, the mean ± SD elimination half-life is 3.51 ± 1.43 hours.
Acetaminophen is metabolized in the liver via cytochrome P450 microsomal enzyme. About 80% to 85% of the acetaminophen in the body is conjugated principally with glucuronic acid and to a lesser extent with sulfuric acid and cysteine. After hepatic conjugation, 90% to 100% of the drug is recovered in the urine within the first day.
About 4% of acetaminophen is metabolized via cytochrome P450 oxidase to a toxic metabolite which is further detoxified by conjugation with glutathione, present in a fixed amount. It is believed that the toxic metabolite NAPQI (N acetyl-p-benzoquinoneimine, N-acetylimidoquinone) is responsible for liver necrosis. High doses of acetaminophen may deplete the glutathione stores so that inactivation of the toxic metabolite is decreased. At high doses, the capacity of metabolic pathways for conjugation with glucuronic acid and sulfuric acid may be exceeded, resulting in increased metabolism of acetaminophen by alternate pathways.

INDICATIONS AND USAGE
Oxycodone and acetaminophen tablets USP are indicated for the relief of moderate to moderately severe pain.

CONTRAINDICATIONS
Oxycodone and acetaminophen tablets should not be administered to patients with known hypersensitivity to oxycodone, acetaminophen, or any other component of this product.
Oxycodone is contraindicated in any situation where opioids are contraindicated including patients with significant respiratory depression (in unmonitored settings or the absence of resuscitative equipment) and patients with acute or severe bronchial asthma or hypercarbia. Oxycodone is contraindicated in the setting of suspected or known paralytic ileus.

WARNINGS
Misuse, Abuse and Diversion of Opioids
Oxycodone is an opioid agonist of the morphine-type. Such drugs are sought by drug abusers and people with addiction disorders and are subject to criminal diversion.
Oxycodone can be abused in a manner similar to other opioid agonists, legal or illicit. This should be considered when prescribing or dispensing oxycodone and acetaminophen tablets in situations where the physician or pharmacist is concerned about an increased risk of misuse, abuse, or diversion. Concerns about misuse, addiction, and diversion should not prevent the proper management of pain.
Healthcare professionals should contact their State Professional Licensing Board or State Controlled Substances Authority for information on how to prevent and detect abuse or diversion of this product.
Administration of oxycodone and acetaminophen tablets should be closely monitored for the following potentially serious adverse reactions and complications:
Respiratory Depression

Respiratory depression is a hazard with the use of oxycodone, one of the active ingredients in oxycodone and acetaminophen tablets, as with all opioid agonists. Elderly and debilitated patients are at particular risk for respiratory depression as are non-tolerant patients given large initial doses of oxycodone or when oxycodone is given in conjunction with other agents that depress respiration. Oxycodone should be used with extreme caution in patients with acute asthma, chronic obstructive pulmonary disorder (COPD), cor pulmonale, or preexisting respiratory impairment. In such patients, even usual therapeutic doses of oxycodone may decrease respiratory drive to the point of apnea. In these patients alternative non-opioid analgesics should be considered, and opioids should be employed only under careful medical supervision at the lowest effective dose.

In case of respiratory depression, a reversal agent such as naloxone hydrochloride may be utilized (see OVERDOSAGE).

Head Injury and Increased Intracranial Pressure

The respiratory depressant effects of opioids include carbon dioxide retention and secondary elevation of cerebrospinal fluid pressure, and may be markedly exaggerated in the presence of head injury, other intracranial lesions or a preexisting increase in intracranial pressure. Oxycodone produces effects on pupillary response and consciousness which may obscure neurologic signs of worsening in patients with head injuries.

Hypotensive Effect

Oxycodone may cause severe hypotension particularly in individuals whose ability to maintain blood pressure has been compromised by a depleted blood volume, or after concurrent administration with drugs which compromise vasomotor tone such as phenothiazines. Oxycodone, like all opioid analgesics of the morphine-type, should be administered with caution to patients in circulatory shock, since vasodilation produced by the drug may further reduce cardiac output and blood pressure. Oxycodone may produce orthostatic hypotension in ambulatory patients.

Hepatotoxicity

Precaution should be taken in patients with liver disease. Hepatotoxicity and severe hepatic failure occurred in chronic alcoholics following therapeutic doses.

PRECAUTIONS
General
Opioid analgesics should be used with caution when combined with CNS depressant drugs, and should be reserved for cases where the benefits of opioid analgesia outweigh the known risks of respiratory depression, altered mental state, and postural hypotension.

Acute Abdominal Conditions – The administration of oxycodone and acetaminophen tablets or other opioids may obscure the diagnosis or clinical course in patients with acute abdominal conditions.

Oxycodone and acetaminophen tablets should be given with caution to patients with CNS depression, elderly or debilitated patients, patients with severe impairment of hepatic, pulmonary, or renal function, hypothyroidism, Addison's disease, prostatic hypertrophy, urethral stricture, acute alcoholism, delirium tremens, kyphoscoliosis with respiratory depression, myxedema, and toxic psychosis.

Oxycodone and acetaminophen tablets may obscure the diagnosis or clinical course in patients with acute abdominal conditions. Oxycodone may aggravate convulsions in patients with convulsive disorders, and all opioids may induce or aggravate seizures in some clinical settings.

Following administration of oxycodone and acetaminophen tablets, anaphylactic reactions have been reported in patients with a known hypersensitivity to codeine, a compound with a structure similar to morphine and oxycodone. The frequency of this possible cross-sensitivity is unknown.

Interactions with Other CNS Depressants

Patients receiving other opioid analgesics, general anesthetics, phenothiazines, other tranquilizers, centrally-acting anti-emetics, sedative-hypnotics or other CNS depressants (including alcohol) concomitantly with oxycodone and acetaminophen tablets may exhibit an additive CNS depression. When such combined therapy is contemplated, the dose of one or both agents should be reduced.

Interactions with Mixed Agonist/Antagonist Opioid Analgesics

Agonist/antagonist analgesics (i.e., pentazocine, nalbuphine, and butorphanol) should be administered with caution to a patient who has received or is receiving a course of therapy with a pure opioid agonist analgesic such as oxycodone. In this situation, mixed agonist/antagonist analgesics may reduce the analgesic effect of oxycodone and/or may precipitate withdrawal symptoms in these patients.

Ambulatory Surgery and Postoperative Use

Oxycodone and other morphine-like opioids have been shown to decrease bowel motility. Ileus is a common postoperative complication, especially after intra-abdominal surgery with use of opioid analgesia. Caution should be taken to monitor for decreased bowel motility in postoperative patients receiving opioids. Standard supportive therapy should be implemented.

Use in Pancreatic/Biliary Tract Disease

Oxycodone may cause spasm of the Sphincter of Oddi and should be used with caution in patients with biliary tract disease, including acute pancreatitis. Opioids like oxycodone may cause increases in the serum amylase level.

Tolerance and Physical Dependence

Tolerance is the need for increasing doses of opioids to maintain a defined effect such as analgesia (in the absence of disease progression or other external factors). Physical dependence is manifested by withdrawal symptoms after abrupt discontinuation of a drug or upon administration of an antagonist. Physical dependence and tolerance are not unusual during chronic opioid therapy.

The opioid abstinence or withdrawal syndrome is characterized by some or all of the following: restlessness, lacrimation, rhinorrhea, yawning, perspiration, chills, myalgia, and mydriasis. Other symptoms also may develop, including: irritability, anxiety, backache, joint pain, weakness, abdominal cramps, insomnia, nausea, anorexia, vomiting, diarrhea, or increased blood pressure, respiratory rate, or heart rate.

In general, opioids should not be abruptly discontinued (see DOSAGE AND ADMINISTRATION; Cessation of Therapy).

Information for Patients/Caregivers

The following information should be provided to patients receiving oxycodone and acetaminophen tablets by their physician, nurse, pharmacist, or caregiver:

1. Patients should be aware that oxycodone and acetaminophen tablets contain oxycodone, which is a morphine-like substance.
2. Patients should be instructed to keep oxycodone and acetaminophen tablets in a secure place out of the reach of children. In the case of accidental ingestions, emergency medical care should be sought immediately.
3. When oxycodone and acetaminophen tablets are no longer needed, the unused tablets should be destroyed by flushing down the toilet.
4. Patients should be advised not to adjust the medication dose themselves. Instead, they must consult with their prescribing physician.
5. Patients should be advised that oxycodone and acetaminophen tablets may impair mental and/or physical ability required for the performance of potentially hazardous tasks (e.g., driving, operating heavy machinery).
6. Patients should not combine oxycodone and acetaminophen tablets with alcohol, opioid analgesics, tranquilizers, sedatives, or other CNS depressants unless under the recommendation and guidance of a physician. When co-administered with another CNS depressant, oxycodone and acetaminophen tablets can cause dangerous additive central nervous system or respiratory depression, which can result in serious injury or death.
7. The safe use of oxycodone and acetaminophen tablets during pregnancy has not been established; thus, women who are planning to become pregnant or are pregnant should consult with their physician before taking oxycodone and acetaminophen tablets.
8. Nursing mothers should consult with their physicians about whether to discontinue nursing or discontinue oxycodone and acetaminophen tablets because of the potential for serious adverse reactions to nursing infants.
9. Patients who are treated with oxycodone and acetaminophen tablets for more than a few weeks should be advised not to abruptly discontinue the medication. Patients should consult with their physician for a gradual discontinuation dose schedule to taper off the medication.
10. Patients should be advised that oxycodone and acetaminophen tablets are a potential drug of abuse. They should protect it from theft, and it should never be given to anyone other than the individual for whom it was prescribed.

Laboratory Tests

Although oxycodone may cross-react with some drug urine tests, no available studies were found which determined the duration of detectability of oxycodone in urine drug screens. However, based on pharmacokinetic data, the approximate duration of detectability for a single dose of oxycodone is roughly estimated to be one to two days following drug exposure.

Urine testing for opiates may be performed to determine illicit drug use and for medical reasons such as evaluation of patients with altered states of consciousness or monitoring efficacy of drug rehabilitation efforts. The preliminary identification of opiates in urine involves the use of an immunoassay screening and thin-layer chromatography (TLC). Gas chromatography/mass spectrometry (GC/MS) may be utilized as a third-stage identification step in the medical investigational sequence for opiate testing after immunoassay and TLC. The identities of 6-keto opiates (e.g., oxycodone) can further be differentiated by the analysis of their methoxime-trimethylsilyl (MO-TMS) derivative.

Drug/Drug Interactions with Oxycodone

Opioid analgesics may enhance the neuromuscular-blocking action of skeletal muscle relaxants and produce an increase in the degree of respiratory depression.

Patients receiving CNS depressants such as other opioid analgesics, general anesthetics, phenothiazines, other tranquilizers, centrally-acting anti-emetics, sedative-hypnotics or other CNS depressants (including alcohol) concomitantly with oxycodone and acetaminophen tablets may exhibit an additive CNS depression. When such combined therapy is contemplated, the dose of one or both agents should be reduced. The concurrent use of anticholinergics with opioids may produce paralytic ileus.

Agonist/antagonist analgesics (i.e., pentazocine, nalbuphine, naltrexone, and butorphanol) should be administered with caution to a patient who has received or is receiving a pure opioid agonist such as oxycodone. These agonist/antagonist analgesics may reduce the analgesic effect of oxycodone or may precipitate withdrawal symptoms.

Drug/Drug Interactions with Acetaminophen

Alcohol, ethyl – Hepatotoxicity has occurred in chronic alcoholics following various dose levels (moderate to excessive) of acetaminophen.

Anticholinergics – The onset of acetaminophen effect may be delayed or decreased slightly, but the ultimate pharmacological effect is not significantly affected by anticholinergics.

Oral Contraceptives – Increase in glucuronidation resulting in increased plasma clearance and a decreased half-life of acetaminophen.

Charcoal (activated) – Reduces acetaminophen absorption when administered as soon as possible after overdose.

Beta Blockers (Propanolol) – Propanolol appears to inhibit the enzyme systems responsible for the glucuronidation and oxidation of acetaminophen. Therefore, the pharmacologic effects of acetaminophen may be increased.

Loop Diuretics – The effects of the loop diuretic may be decreased because acetaminophen may decrease renal prostaglandin excretion and decrease plasma renin activity.

Lamotrigine– Serum lamotrigine concentrations may be reduced, producing a decrease in therapeutic effects.

Probenecid – Probenecid may increase the therapeutic effectiveness of acetaminophen slightly.

Zidovudine – The pharmacologic effects of zidovudine may be decreased because of enhanced nonhepatic or renal clearance of zidovudine.

Drug/Laboratory Test Interactions

Depending on the sensitivity/specificity and the test methodology, the individual components of oxycodone and acetaminophen tablets may cross-react with assays used in the preliminary detection of cocaine (primary urinary metabolite, benzoylecgonine) or marijuana (cannabinoids) in human urine. A more specific alternate chemical method must be used in order to obtain a confirmed analytical result. The preferred confirmatory method is gas chromatography/mass spectrometry (GC/MS). Moreover, clinical considerations and professional judgment should be applied to any drug-of-abuse test result, particularly when preliminary positive results are used.

Acetaminophen may interfere with home blood glucose measurement systems; decreases of > 20% in mean glucose values may be noted. This effect appears to be drug, concentration and system dependent.

Carcinogenesis, Mutagenesis, Impairment of Fertility

Carcinogenesis – Animal studies to evaluate the carcinogenic potential of oxycodone and acetaminophen have not been performed.

Mutagenesis – The combination of oxycodone and acetaminophen has not been evaluated for mutagenicity. Oxycodone alone was negative in a bacterial reverse mutation assay (Ames), an in vitro chromosome aberration assay with human lymphocytes without metabolic activation and an in vivo mouse micronucleus assay. Oxycodone was clastogenic in the human lymphocyte chromosomal assay in the presence of metabolic activation and in the mouse lymphoma assay with or without metabolic activation.

Fertility – Animal studies to evaluate the effects of oxycodone on fertility have not been performed.

Pregnancy

Teratogenic Effects. Pregnancy Category C – Animal reproductive studies have not been conducted with oxycodone and acetaminophen. It is also not known whether oxycodone and acetaminophen tablets can cause fetal harm when administered to a pregnant woman or can affect reproductive capacity. Oxycodone and acetaminophen tablets should not be given to a pregnant woman unless in the judgment of the physician, the potential benefits outweigh the possible hazards.

Nonteratogenic Effects – Opioids can cross the placental barrier and have the potential to cause neonatal respiratory depression. Opioid use during pregnancy may result in a physically drug-dependent fetus. After birth, the neonate may suffer severe withdrawal symptoms.

Labor and Delivery

Oxycodone and acetaminophen tablets are not recommended for use in women during and immediately prior to labor and delivery due to its potential effects on respiratory function in the newborn.

Nursing Mothers

Ordinarily, nursing should not be undertaken while a patient is receiving oxycodone and acetaminophen tablets because of the possibility of sedation and/or respiratory depression in the infant. Oxycodone is excreted in breast milk in low concentrations, and there have been rare reports of somnolence and lethargy in babies of nursing mothers taking an oxycodone/acetaminophen product. Acetaminophen is also excreted in breast milk in low concentrations.

Pediatric Use

Safety and effectiveness in pediatric patients have not been established.

Geriatric Use

Special precaution should be given when determining the dosing amount and frequency of oxycodone and acetaminophen tablets for geriatric patients, since clearance of oxycodone may be slightly reduced in this patient population when compared to younger patients.

Hepatic Impairment

In a pharmacokinetic study of oxycodone in patients with end-stage liver disease, oxycodone plasma clearance decreased and the elimination half-life increased. Care should be exercised when oxycodone is used in patients with hepatic impairment.

Renal Impairment

In a study of patients with end stage renal impairment, mean elimination half-life was prolonged in uremic patients due to increased volume of distribution and reduced clearance. Oxycodone should be used with caution in patients with renal impairment.

ADVERSE REACTIONS
Serious adverse reactions that may be associated with oxycodone and acetaminophen tablet use include respiratory depression, apnea, respiratory arrest, circulatory depression, hypotension, and shock (see OVERDOSAGE).

The most frequently observed non-serious adverse reactions include lightheadedness, dizziness, drowsiness or sedation, nausea, and vomiting. These effects seem to be more prominent in ambulatory than in nonambulatory patients, and some of these adverse reactions may be alleviated if the patient lies down. Other adverse reactions include euphoria, dysphoria, constipation, and pruritus.

Hypersensitivity reactions may include: Skin eruptions, urticarial, erythematous skin reactions. Hematologic reactions may include: Thrombocytopenia, neutropenia, pancytopenia, hemolytic anemia. Rare cases of agranulocytosis have likewise been associated with acetaminophen use. In high doses, the most serious adverse effect is a dose-dependent, potentially fatal hepatic necrosis. Renal tubular necrosis and hypoglycemic coma also may occur.

Other adverse reactions obtained from postmarketing experiences with oxycodone and acetaminophen tablets are listed by organ system and in decreasing order of severity and/or frequency as follows:

Body as a Whole

Anaphylactoid reaction, allergic reaction, malaise, asthenia, fatigue, chest pain, fever, hypothermia, thirst, headache, increased sweating, accidental overdose, non-accidental overdose

Cardiovascular

Hypotension, hypertension, tachycardia, orthostatic hypotension, bradycardia, palpitations, dysrhythmias

Central and Peripheral Nervous System

Stupor, tremor, paraesthesia, hypoaesthesia, lethargy, seizures, anxiety, mental impairment, agitation, cerebral edema, confusion, dizziness

Fluid and Electrolyte

Dehydration, hyperkalemia, metabolic acidosis, respiratory alkalosis

Gastrointestinal

Dyspepsia, taste disturbances, abdominal pain, abdominal distention, sweating increased, diarrhea, dry mouth, flatulence, gastro-intestinal disorder, nausea, vomiting, pancreatitis, intestinal obstruction, ileus

Hepatic

Transient elevations of hepatic enzymes, increase in bilirubin, hepatitis, hepatic failure, jaundice, hepatotoxicity, hepatic disorder

Hearing and Vestibular

Hearing loss, tinnitus

Hematologic

Thrombocytopenia

Hypersensitivity

Acute anaphylaxis, angioedema, asthma, bronchospasm, laryngeal edema, urticaria, anaphylactoid reaction

Metabolic and Nutritional

Hypoglycemia, hyperglycemia, acidosis, alkalosis

Musculoskeletal

Myalgia, rhabdomyolysis

Ocular

Miosis, visual disturbances, red eye

Psychiatric

Drug dependence, drug abuse, insomnia, confusion, anxiety, agitation, depressed level of consciousness, nervousness, hallucination, somnolence, depression, suicide

Respiratory System

Bronchospasm, dyspnea, hyperpnea, pulmonary edema, tachypnea, aspiration, hypoventilation, laryngeal edema

Skin and Appendages

Erythema, urticaria, rash, flushing

Urogenital

Interstitial nephritis, papillary necrosis, proteinuria, renal insufficiency and failure, urinary retention

DRUG ABUSE AND DEPENDENCE

Oxycodone and acetaminophen tablets are a Schedule II controlled substance. Oxycodone is a mu-agonist opioid with an abuse liability similar to morphine. Oxycodone, like morphine and other opioids used in analgesia, can be abused and is subject to criminal diversion.

Drug addiction is defined as an abnormal, compulsive use, use for non-medical purposes of a substance despite physical, psychological, occupational or interpersonal difficulties resulting from such use, and continued use despite harm or risk of harm. Drug addiction is a treatable disease, utilizing a multi-disciplinary approach, but relapse is common. Opioid addiction is relatively rare in patients with chronic pain but may be more common in individuals who have a past history of alcohol or substance abuse or dependence. Pseudoaddiction refers to pain relief seeking behavior of patients whose pain is poorly managed. It is considered an iatrogenic effect of ineffective pain management. The health care provider must assess continuously the psychological and clinical condition of a pain patient in order to distinguish addiction from pseudoaddiction and thus, be able to treat the pain adequately.

Physical dependence on a prescribed medication does not signify addiction. Physical dependence involves the occurrence of a withdrawal syndrome when there is sudden reduction or cessation in drug use or if an opiate antagonist is administered. Physical dependence can be detected after a few days of opioid therapy. However, clinically significant physical dependence is only seen after several weeks of relatively high dosage therapy. In this case, abrupt discontinuation of the opioid may result in a withdrawal syndrome. If the discontinuation of opioids is therapeutically indicated, gradual tapering of the drug over a 2-week period will prevent withdrawal symptoms. The severity of the withdrawal syndrome depends primarily on the daily dosage of the opioid, the duration of therapy and medical status of the individual.

The withdrawal syndrome of oxycodone is similar to that of morphine. This syndrome is characterized by yawning, anxiety, increased heart rate and blood pressure, restlessness, nervousness, muscle aches, tremor, irritability, chills alternating with hot flashes, salivation, anorexia, severe sneezing, lacrimation, rhinorrhea, dilated pupils, diaphoresis, piloerection, nausea, vomiting, abdominal cramps, diarrhea and insomnia, and pronounced weakness and depression.

“Drug-seeking” behavior is very common in addicts and drug abusers. Drug-seeking tactics include emergency calls or visits near the end of office hours, refusal to undergo appropriate examination, testing or referral, repeated “loss” of prescriptions, tampering with prescriptions and reluctance to provide prior medical records or contact information for other treating physician(s). “Doctor Shopping” to obtain additional prescriptions is common among drug abusers and people suffering from untreated infection.

Abuse and addiction are separate and distinct from physical dependence and tolerance. Physicians should be aware that addiction may not be accompanied by concurrent tolerance and symptoms of physical dependence in all addicts. In addition, abuse of opioids can occur in the absence of true addiction and is characterized by misuse for non-medical purposes, often in combination with other psychoactive substances. Oxycodone, like other opioids, has been diverted for non-medical use. Careful record-keeping of prescribing information, including quantity, frequency, and renewal requests is strongly advised.

Proper assessment of the patient, proper prescribing practices, periodic re-evaluation of therapy, and proper dispensing and storage are appropriate measures that help to limit abuse of opioid drugs.

Like other opioid medications, oxycodone and acetaminophen tablets are subject to the Federal Controlled Substances Act. After chronic use, oxycodone and acetaminophen tablets should not be discontinued abruptly when it is thought that the patient has become physically dependent on oxycodone.

Interactions with Alcohol and Drugs of Abuse

Oxycodone may be expected to have additive effects when used in conjunction with alcohol, other opioids, or illicit drugs that cause central nervous system depression.

OVERDOSAGE

Enter section text here

DOSAGE AND ADMINISTRATION
Dosage should be adjusted according to the severity of the pain and the response of the patient. It may occasionally be necessary to exceed the usual dosage recommended below in cases of more severe pain or in those patients who have become tolerant to the analgesic effect of opioids. If pain is constant, the opioid analgesic should be given at regular intervals on an around-the-clock schedule. Oxycodone and acetaminophen tablets are given orally.
The total daily dose of acetaminophen should not exceed 4 grams.

Strength | Usual Adult Dosage | Maximal Daily Dose
Oxycodone and acetaminophen tablets 5 mg/325 mg | 1 tablet every 6 hours as needed for pain | 12 Tablets
Oxycodone and acetaminophen tablets 7.5 mg/325 mg | 1 tablet every 6 hours as needed for pain | 8 Tablets
Oxycodone and acetaminophen tablets 7.5 mg/500 mg | 1 tablet every 6 hours as needed for pain | 8 Tablets
Oxycodone and acetaminophen tablets 10 mg/325 mg | 1 tablet every 6 hours as needed for pain | 6 Tablets

Cessation of Therapy

In patients treated with oxycodone and acetaminophen tablets for more than a few weeks who no longer require therapy, doses should be tapered gradually to prevent signs and symptoms of withdrawal in the physically dependent patient.

HOW SUPPLIED

Each oxycodone and acetaminophen tablet USP 5 mg/325 mg contains oxycodone hydrochloride 5 mg (equivalent to 4.4815 mg oxycodone) and acetaminophen 325 mg. It is available as a round, white scored tablet debossed with a 512 identification number.

49999-852-14

49999-852-30

49999-852-60

49999-852-90

Each oxycodone and acetaminophen tablet USP 7.5 mg/325 mg contains oxycodone hydrochloride 7.5 mg (equivalent to 6.7228 mg oxycodone) and acetaminophen 325 mg. It is available as a white to off-white caplet shaped tablet debossed with “M522” on one side and “7.5/325” on the other side.

Each oxycodone and acetaminophen tablet USP 7.5 mg/500 mg contains oxycodone hydrochloride 7.5 mg (equivalent to 6.7228 mg oxycodone) and acetaminophen 500 mg. It is available as a white to off-white oval shaped tablet debossed with “M582” on one side and the other side is plain.

Each oxycodone and acetaminophen tablet USP 10 mg/325 mg contains oxycodone hydrochloride 10 mg (equivalent to 8.9637 mg oxycodone) and acetaminophen 325 mg. It is available as a white to off-white caplet shaped tablet debossed with “M523” on one side and “10/325” on the other side.

Store at 20° to 25°C (68° to 77°F) [see USP Controlled Room Temperature].

Dispense in a tight, light-resistant container as defined in the USP, with a child-resistant closure (as required).

DEA Order Form Required.

Mallinckrodt Inc.,
Hazelwood, MO 63042 USA.

Printed in U.S.A.

COVIDIEN™
Mallinckrodt

Rev 05/2009

PACKAGE LABEL - PRINCIPAL DISPLAY PANEL - 5 mg*/325 mg Bottle

Multiple strengths. Do not dispense unless strength is stated.
NDC 0406-0512-05
500 TABLETS
OXYCODONE AND ACETAMINOPHEN TABLETS USP
CII
5 mg*/325 mg
Each tablet contains:
Oxycodone Hydrochloride USP. . . . . . . 5 mg*
Acetaminophen USP . . . . . . . . . . . . . .325 mg
Rx only
Mallinckrodt